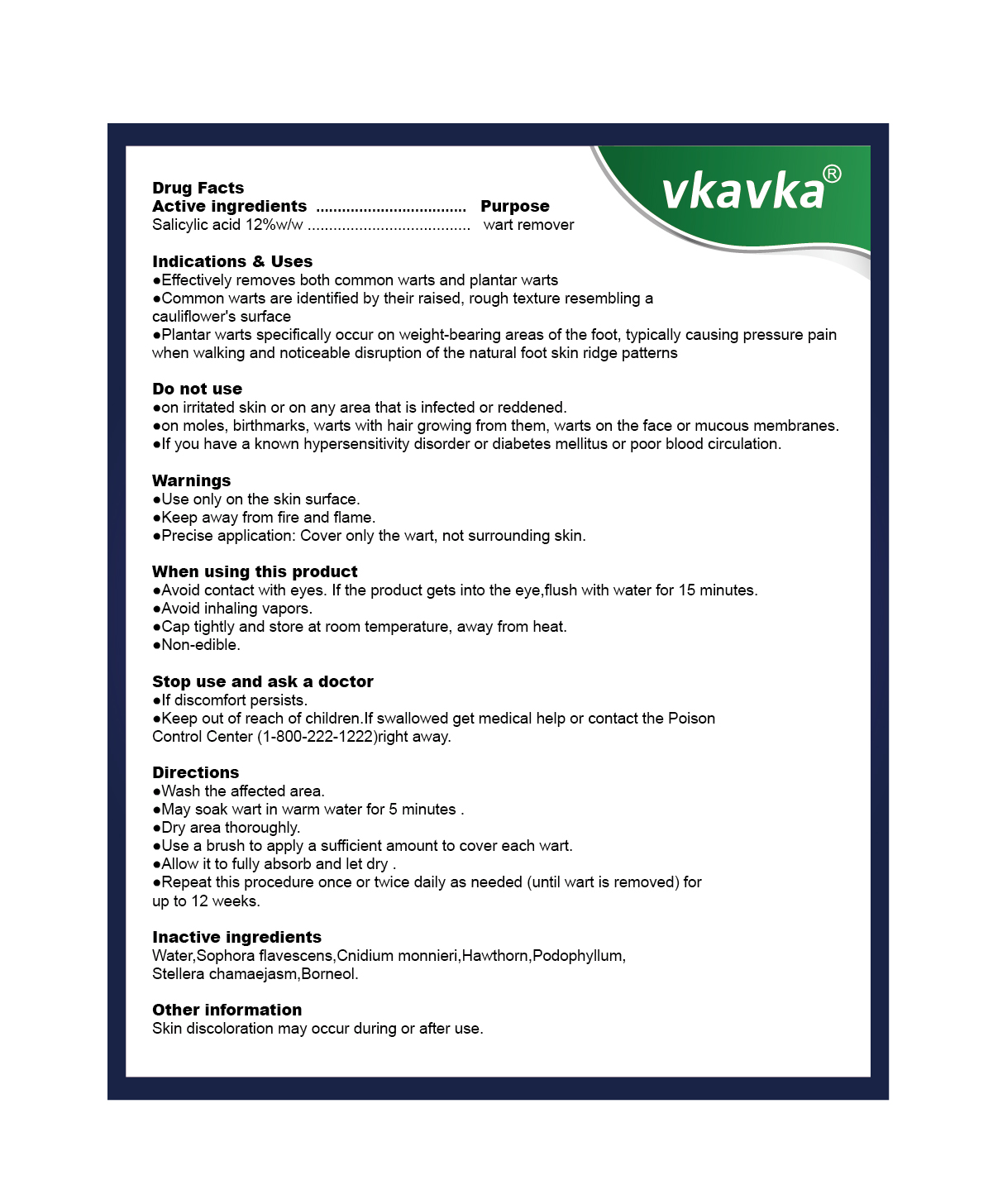 DRUG LABEL: vkavka Wart Remover
NDC: 87386-001 | Form: LIQUID
Manufacturer: Shenzhen Lanxi Trading Co., Ltd.
Category: otc | Type: HUMAN OTC DRUG LABEL
Date: 20260129

ACTIVE INGREDIENTS: SALICYLIC ACID 0.12 g/1 mL
INACTIVE INGREDIENTS: WATER; PODOPHYLLUM; SOPHORA FLAVESCENS ROOT; STELLERA CHAMAEJASME WHOLE; CNIDIUM MONNIERI WHOLE; BORNEOL; HAWTHORN LEAF WITH FLOWER

87386-001 vkavka Wart Remover

ACTIVE INGREDIENT

Salicylic acid 12%

PURPOSE

wart remover

INDICATIONS AND USAGE

Effectively removes both common warts and plantar warts
Common warts are identified by their raised, rough texture resembling a cauliflower's surface
Plantar warts specifically occur on weight-bearing areas of the foot, typically causing pressure pain when walking and noticeable disruption of the natural foot skin ridge patterns

WARNINGS

Use only on the skin surface.

Keep away from fire and flame

Precise application: Cover only the wart, not surrounding skin

DO NOT USE

on irritated skin or on any area that is infected or reddened.
on moles, birthmarks, warts with hair growing from them, warts on the face or mucous membranes.
lf you have a known hypersensitivity disorder or diabetes mellitus or poor blood circulation.

WHEN USING

Avoid contact with eyes. lf the product gets into the eye,flush with water for 15 minutes.
Avoid inhaling vapors.
Cap tightly and store at room temperature, away from heat.
Non-edible.

STOP USE

lf discomfort persists.

Keep out of reach of children.lf swallowed get medical help or contact the Poison Control Center(1-800-222-1222)right away.

DOSAGE AND ADMINISTRATION

Wash the affected area.
May soak wart in warm water for 5 minutese
Dry area thoroughly.
Use a brush to apply a sufficient amount to cover each wart.
Allow it to fully absorb and let dry .
Repeat this procedure once or twice daily as needed (until wart is removed) for up to 12 weeks.

INACTIVE INGREDIENT

Water
Sophora flavescens root
Cnidium monnieri whole
Hawthorn leaf with flower
Podophyllum
Stellera chamaejasm whole
Borneol